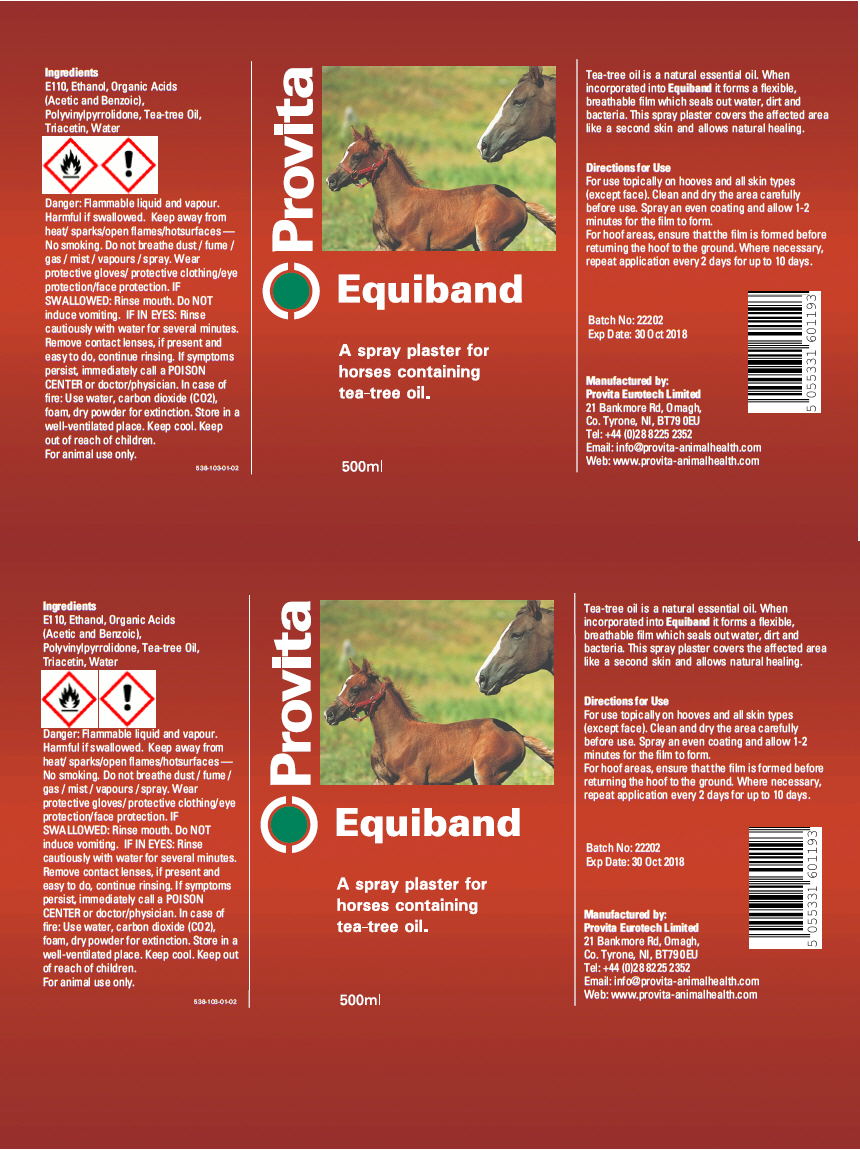 DRUG LABEL: Provita Equiband
NDC: 16371-105 | Form: SPRAY
Manufacturer: Provita Eurotech Ltd
Category: animal | Type: OTC ANIMAL DRUG LABEL
Date: 20181217

ACTIVE INGREDIENTS: Benzoic acid 74 g/1 L

Provita Equiband

DESCRIPTION

Ingredients

E110, Ethanol, Organic Acids (Acetic and Benzoic), Polyvinylpyrrolidone, Tea-tree Oil, Triacetin, Water

Tea-tree oil is a natural essential oil. When incorporated into Equiband it forms a flexible, breathable film which seals out water, dirt and bacteria. This spray plaster covers the affected area like a second skin and allows natural healing.

PRECAUTIONS

Danger: Flammable liquid and vapour. Harmful if swallowed. Keep away from heat/ sparks/open flames/hotsurfaces — No smoking. Do not breathe dust / fume / gas / mist / vapours / spray. Wear protective gloves/ protective clothing/eye protection/face protection. IF SWALLOWED: Rinse mouth. Do NOT induce vomiting. IF IN EYES: Rinse cautiously with water for several minutes. Remove contact lenses, if present and easy to do, continue rinsing. If symptoms persist, immediately call a POISON CENTER or doctor/physician. In case of fire: Use water, carbon dioxide (CO2), foam, dry powder for extinction. Store in a well-ventilated place. Keep cool. Keep out of reach of children.

For animal use only.

DOSAGE AND ADMINISTRATION

Directions for Use

For use topically on hooves and all skin types (except face). Clean and dry the area carefully before use. Spray an even coating and allow 1-2 minutes for the film to form.

For hoof areas, ensure that the film is formed before returning the hoof to the ground. Where necessary, repeat application every 2 days for up to 10 days.

PRINCIPAL DISPLAY PANEL - 500 ml Bottle Label

Provita

Equiband

A spray plaster for
horses containing
tea-tree oil.

500ml